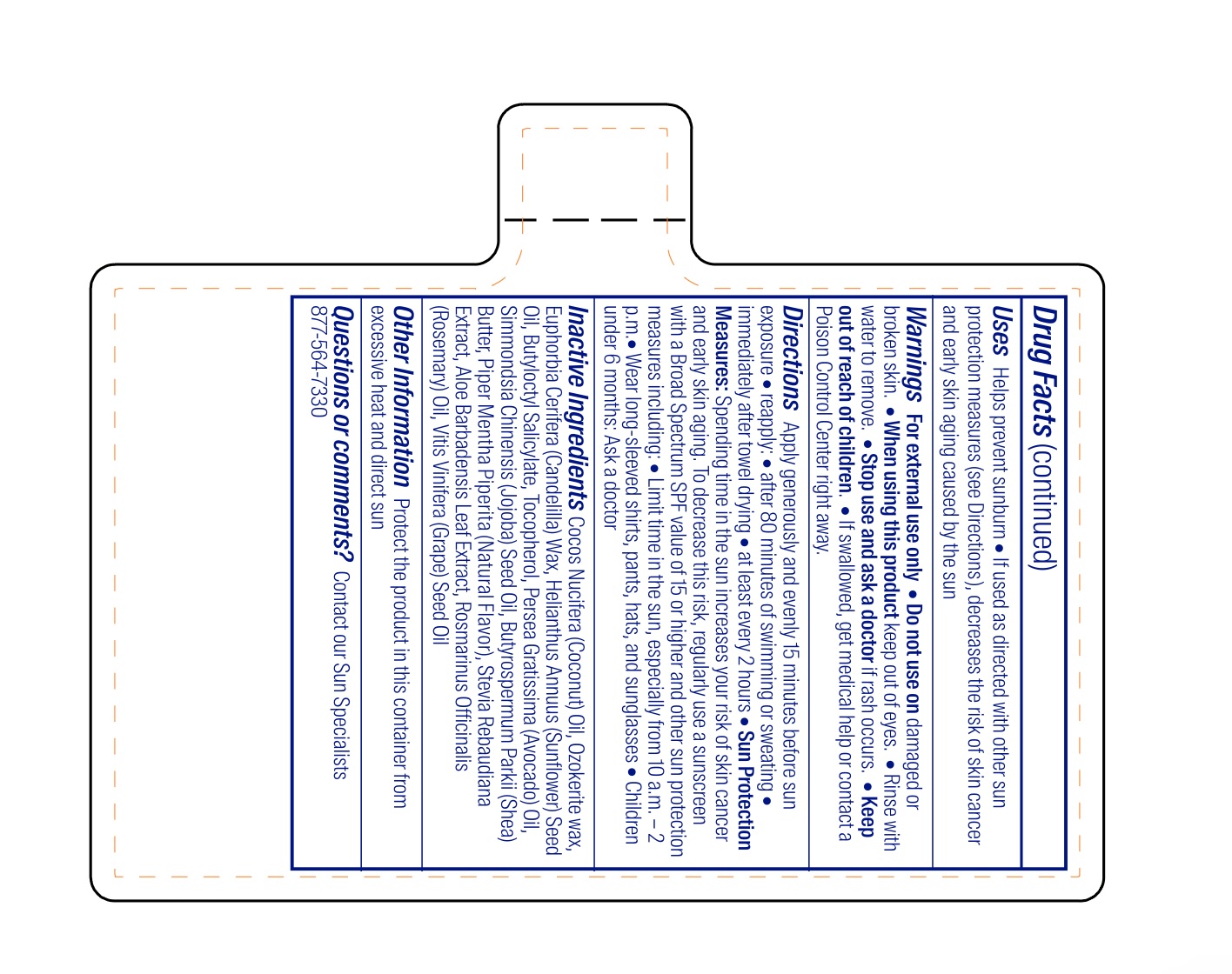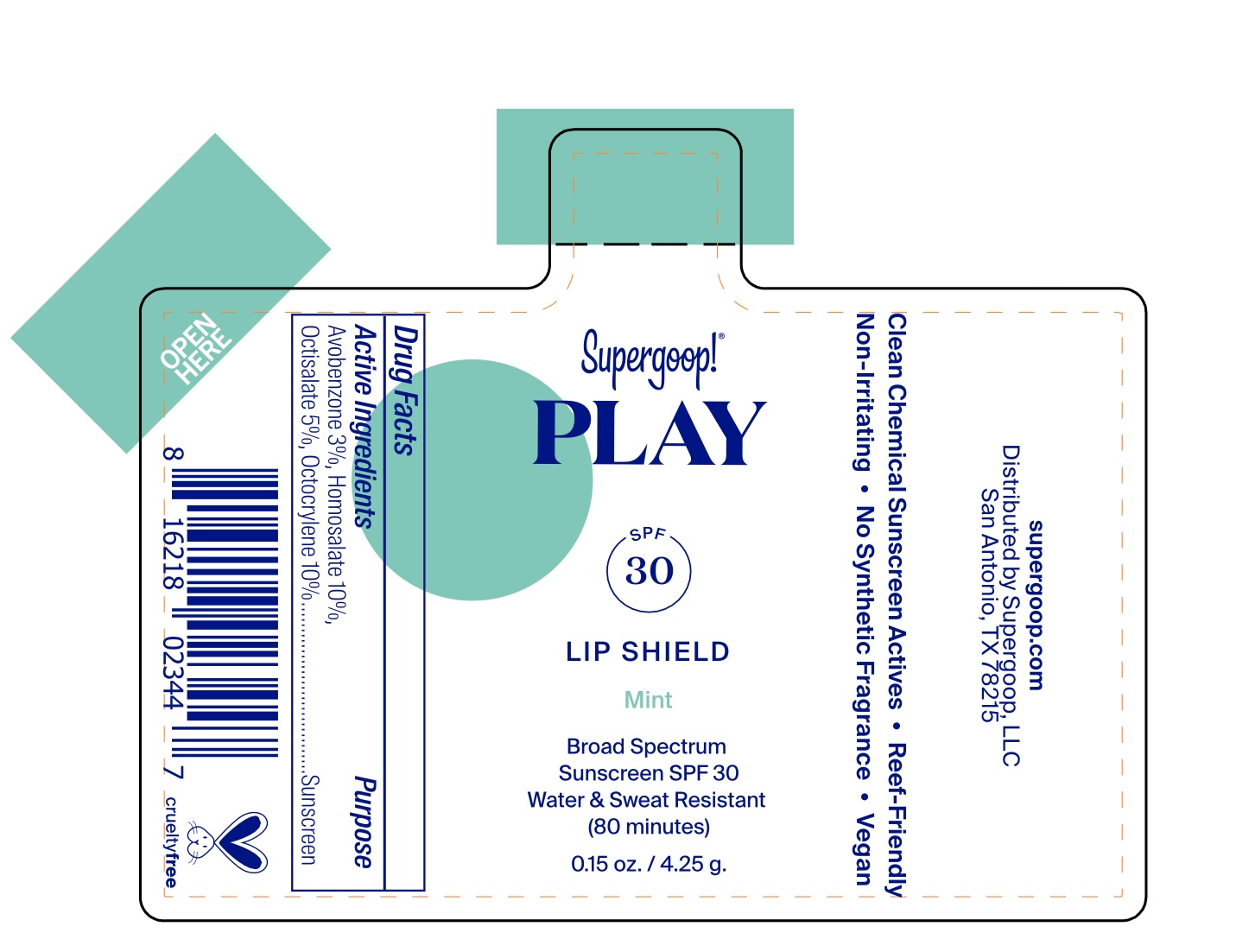 DRUG LABEL: PLAY Lip Shield SPF 30 - Mint
NDC: 75936-658 | Form: STICK
Manufacturer: Supergoop LLC
Category: otc | Type: HUMAN OTC DRUG LABEL
Date: 20250818

ACTIVE INGREDIENTS: AVOBENZONE 3 g/100 g; OCTISALATE 5 g/100 g; OCTOCRYLENE 10 g/100 g; HOMOSALATE 10 g/100 g
INACTIVE INGREDIENTS: COCOS NUCIFERA (COCONUT) OIL; BUTYLOCTYL SALICYLATE; SIMMONDSIA CHINENSIS (JOJOBA) SEED OIL; BUTYROSPERMUM PARKII (SHEA) BUTTER; STEVIA REBAUDIANA LEAF; ALOE BARBADENSIS LEAF JUICE; MENTHA PIPERITA; ROSMARINUS OFFICINALIS (ROSEMARY) LEAF OIL; CERESIN; TOCOPHEROL; EUPHORBIA CERIFERA (CANDELILLA) WAX; HELIANTHUS ANNUUS (SUNFLOWER) SEED OIL; PERSEA GRATISSIMA (AVOCADO) OIL; VITIS VINIFERA (GRAPE) SEED OIL

PLAY Lip Shield SPF 30 - Mint

ACTIVE INGREDIENT

Active Ingredients: Avobenzone 3%, Homosalate 10%, Octisalate 5%, Octocrylene 10%

PURPOSE

Helps prevent sunburn

If used as directed with other sun protection measures (see Directions), decreases the risk of skin cancer and early skin aging caused by the sun

Warnings

• For external use only. • Do not use on damaged or broken skin. • When using this product keep out of eyes. Rinse with water to remove.

Keep out of reach of children. If product is swallowed, get medical help, or contact a poison control center right away.

Stop use and ask a doctor if rash occurs

Directions

• Apply generously and evenly as the last step in your skincare routine, before makeup and 15 minutes before sun exposure. • Reapply: • after 80 minutes of swimming or sweating. • immediately after towel drying • at least every 2 hours. • Children under 6 months of age: ask a doctor. • Sun Protection Measures. Spending time in the sun increases your risk of skin cancer and early skin aging. To decrease this risk, regularly use a sunscreen with a Broad Spectrum SPF value of 15 or higher and other sun protection measures including: • limit time in the sun, especially from 10 a.m.-2 p.m. • wear long-sleeved shirts, pants, hats, and sunglasses.

INACTIVE INGREDIENT

Inactive Ingredients: Cocos Nucifera (Coconut) Oil, Ozokerite wax, Euphorbia Cerifera (Candelilla) Wax, Helianthus Annuus (Sunflower) Seed Oil, Butyloctyl Salicylate, Tocopherol, Glycine Soja (Soybean) Oil, Persea Gratissima (Avocado) Oil, Simmondsia Chinensis (Jojoba) Seed Oil, Butyrospermum Parkii (Shea) Butter, Piper Mentha Piperita (Natural Flavor), Stevia Rebaudiana Extract, Aloe Barbadensis Leaf Extract, Rosmarinus Officinalis (Rosemary) Oil, Vitis Vinifera (Grape) Seed Oil

PACKAGE LABEL

PLAY

SPF 30

Lip Shield

Mint

Broad Spectrum

Sunscreen SPF 30

Water & Sweat Resistant

(80 minutes)

0.15 oz. / 4.25 g.